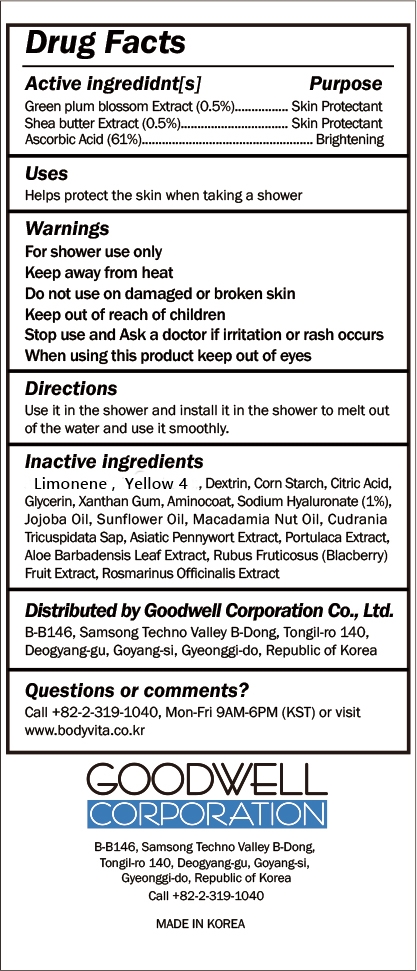 DRUG LABEL: BodyVita Shower Filter
NDC: 82221-102 | Form: JELLY
Manufacturer: Goodwell Corporation Co., Ltd.
Category: otc | Type: HUMAN OTC DRUG LABEL
Date: 20231005

ACTIVE INGREDIENTS: SHEANUT OIL 0.005 g/100 g; PRUNUS MUME FLOWER OIL 0.005 g/100 g; ASCORBIC ACID 0.61 g/100 g
INACTIVE INGREDIENTS: ICODEXTRIN; STARCH, CORN; MACLURA TRICUSPIDATA WHOLE; XANTHAN GUM; LIMONENE, (+)-; P-NITROBIPHENYL; BETAINE; HYALURONATE SODIUM; GLYCERIN; JOJOBA OIL; SUNFLOWER OIL; PURSLANE; BLACKBERRY; CENTELLA ASIATICA WHOLE; CITRIC ACID MONOHYDRATE; MACADAMIA OIL; ALOE VERA LEAF; ROSEMARY

82221-102 Bodyvita: Shower Filter

Active Ingredients

Vitamin-C (Ascorbic Acid) 61%

Green plum blossom Extract 0.5%

Shea Butter Extract 0.5%

Purposes

Skin Protectant

Brightening

Uses

Helps protect the skin when taking a shower

Warnings

Keep out of reach of children

Warnings

Do not use on damaged or broken skin

Warnings

Stop use and ask a doctor if irritation or rash occurs

Warnings

When using this product keep out of eyes

Warnings

For shower use only

Keep away from heat

Directions

Use it in the shower and install it in the shower to melt out of the water and use it smoothly.

Inactive Ingredients

Limonene, Yellow 4, Dextrin, Corn Starch, Citric Acid, Glycerin, Xanthan gum, Aminocoat, Sodium Hyaluronate, Vitamin-C (Ascorbic Acid), Green plum blossom Extract, Shea butter Extract, Jojoba oil, Sunflower oil, Macadamia nut oil, cudrania tricuspidata Sap, Asiatic pennywort Extract, Portulaca Extract, Aloe Barbadensis Leaf Extract, Rubus Fruticosus(Blacberry)Fruit Extract, Rosmarinus Officinalis (Rosemary) Extract